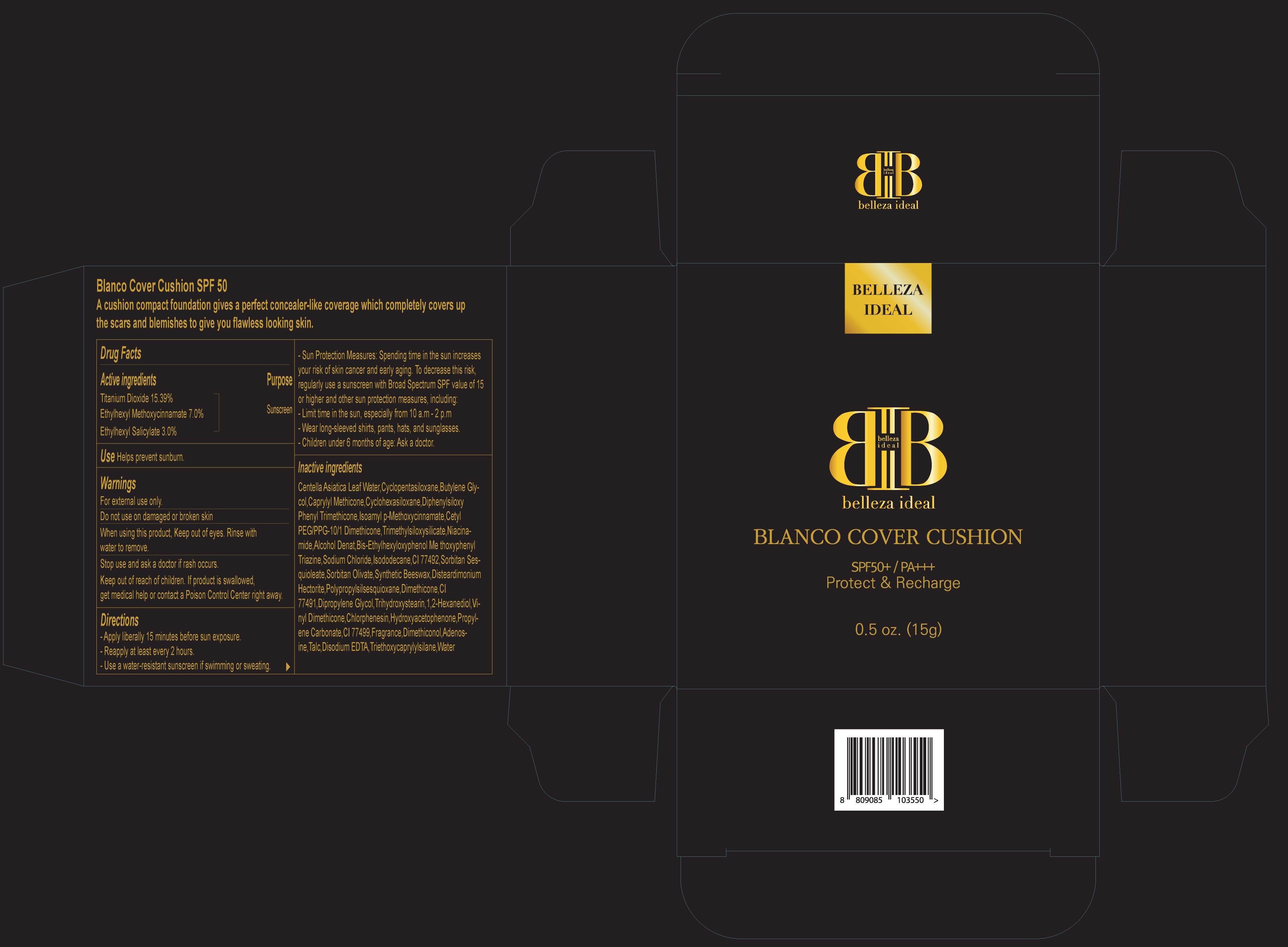 DRUG LABEL: BELLEZA IDEAL Blanco Cover Cushion
NDC: 90007-020 | Form: POWDER
Manufacturer: Belleza Ideal
Category: otc | Type: HUMAN OTC DRUG LABEL
Date: 20200803

ACTIVE INGREDIENTS: Titanium Dioxide 15.39 g/100 g; OCTINOXATE 7.0 g/100 g; OCTISALATE 3.0 g/100 g
INACTIVE INGREDIENTS: CENTELLA ASIATICA LEAF; CYCLOMETHICONE 5; Butylene Glycol

ACTIVE INGREDIENT

Titanium Dioxide 15.39%
Ethylhexyl Methoxycinnamate 7.0%
Ethylhexyl Salicylate 3.0%

INACTIVE INGREDIENTS

Centella Asiatica Leaf Water,Cyclopentasiloxane,Butylene Glycol,Caprylyl Methicone,Cyclohexasiloxane,Diphenylsiloxy Phenyl Trimethicone,Isoamyl p-Methoxycinnamate,Cetyl PEG/PPG-10/1 Dimethicone,Trimethylsiloxysilicate,Niacinamide,Alcohol Denat,Bis-Ethylhexyloxyphenol Methoxyphenyl Triazine,Sodium Chloride,Isododecane,CI 77492,Sorbitan Sesquioleate,Sorbitan Olivate,Synthetic Beeswax,Disteardimonium Hectorite,Polypropylsilsesquioxane,Dimethicone,CI 77491,Dipropylene Glycol,Trihydroxystearin,1,2-Hexanediol,Vinyl Dimethicone,Chlorphenesin,Hydroxyacetophenone,Propylene Carbonate,CI 77499,Fragrance,Dimethiconol,Adenosine,Talc,Disodium EDTA,Triethoxycaprylylsilane,Water

PURPOSE

Sunscreen

WARNINGS

For external use only.
- Do not use on damaged or broken skin
- When using this product, Keep out of eyes. Rinse with water to remove.
- Stop use and ask a doctor if rash occurs.
- Keep out of reach of children. If product is swallowed, get medical help or contact a Poison Control Center right away.

DESCRIPTION

Uses:
Helps prevent sunburn.

Directions:
-Apply liberally 15 minutes before sun exposure.
-Reapply at least every 2 hours.
-Use a water-resistant sunscreen if swimming or sweating.
-Sun Protection Measures: Spending time in the sun increases your risk of skin cancer and early aging. To decrease this risk, regularly use a sunscreen with Broad Spectrum SPF value of 15 or higher and other sun protection measures, including:
Limit time in the sun, especially from 10 a.m - 2 p.m
Wear long-sleeved shirts, pants, hats, and sunglasses.
Children under 6 months of age: Ask a doctor.